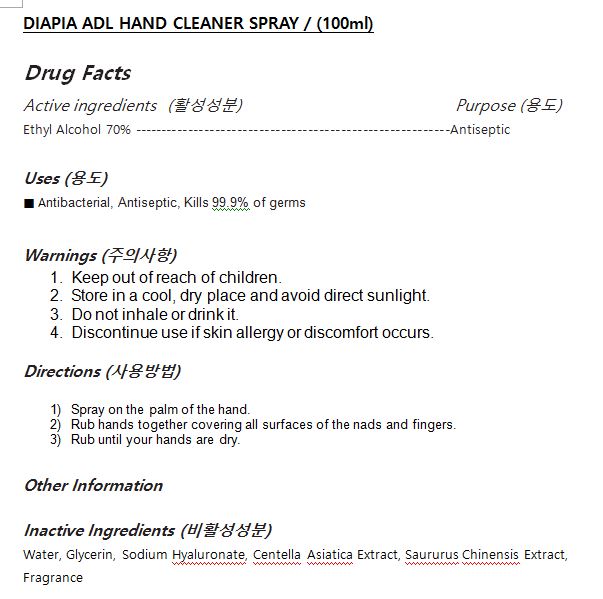 DRUG LABEL: DIAPIA ADL HAND CLEANERSPRAY
NDC: 71857-0015 | Form: SPRAY
Manufacturer: BSG H & B Co., Ltd.
Category: otc | Type: HUMAN OTC DRUG LABEL
Date: 20201029

ACTIVE INGREDIENTS: ALCOHOL 70 mL/100 mL
INACTIVE INGREDIENTS: WATER

Drug Facts

INACTIVE INGREDIENT

Water, Glycerin, Sodium Hyaluronate, Centella Asiatica Extract, Saururus Chinensis Extract, Fragrance

PURPOSE

Antibacterial, Antiseptic, Kills 99.9% of germs

keep out of reach of the children

INDICATIONS AND USAGE

Spray on the palm of the hand.

Rub hands together covering all surfaces of the nads and fingers.

Rub until your hands are dry.

Keep out of reach of children.

Store in a cool, dry place and avoid direct sunlight.

Do not inhale or drink it.

Discontinue use if skin allergy or discomfort occurs.

DOSAGE AND ADMINISTRATION

for external use only